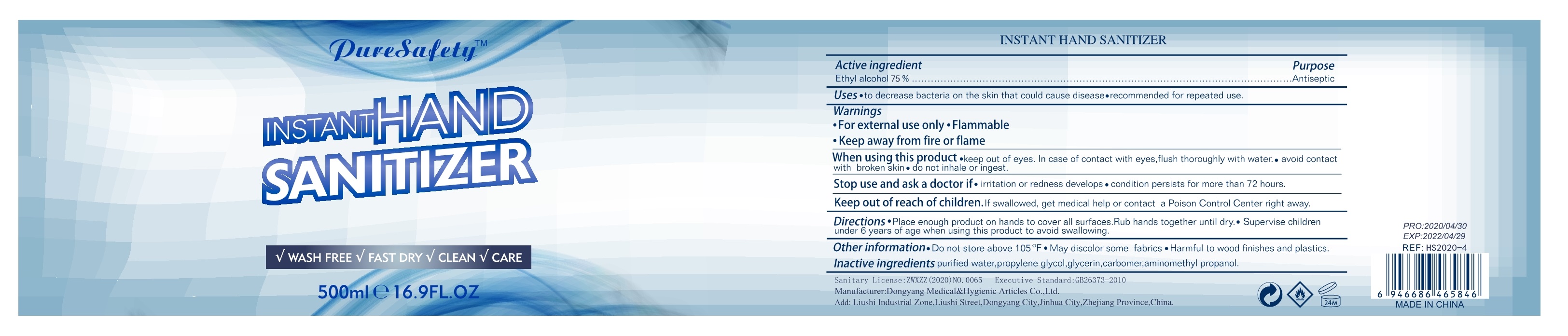 DRUG LABEL: Hand Sanitizer Gel
NDC: 10079-500 | Form: GEL
Manufacturer: HOMELIKE INC
Category: otc | Type: HUMAN OTC DRUG LABEL
Date: 20200723

ACTIVE INGREDIENTS: ALCOHOL 375 mL/500 mL
INACTIVE INGREDIENTS: GLYCERIN; AMINOMETHYLPROPANOL; WATER; PROPYLENE GLYCOL; CARBOMER 980

10079-500 dongyang medical 53031-022 500ml 75%

Active Ingredient(s)

Alcohol 75% v/v. Purpose: Antiseptic

Purpose

Antiseptic, Hand Sanitizer

Use

To decrease bacteria on the skin that could cause disease.

Recommended for repeated use.

Warnings

For external use only. Flammable. Keep away from heat or flame

Do not use

- in children less than 2 months of age
- on open skin wounds

WHEN USING

keep out of eyes. In case of contact with eyes, flush thoroughly with water.

avoid contact with broken skin.

do not inhale or ingest.

Stop use and ask a doctor if irritation or redness develops.

condition persists for more than 72 hours.

Keep out of reach of children. If swallowed, get medical help or contact a Poison Control Center right away.

Directions

- Place enough product on hands to cover all surfaces. Rub hands together until dry.
- Supervise children under 6 years of age when using this product to avoid swallowing.

Other information

- Do not store above 105F
- May discolor some fabrics.
- Harmful to wood finishes and plastics.

Inactive ingredients

AMINOMETHYLPROPANOL ,CARBOMER,GLYCERIN ,PROPYLENE GLYCOL, WATER

Package Label - Principal Display Panel

500 ml in 1 BOTTLE NDC:10079-500-01